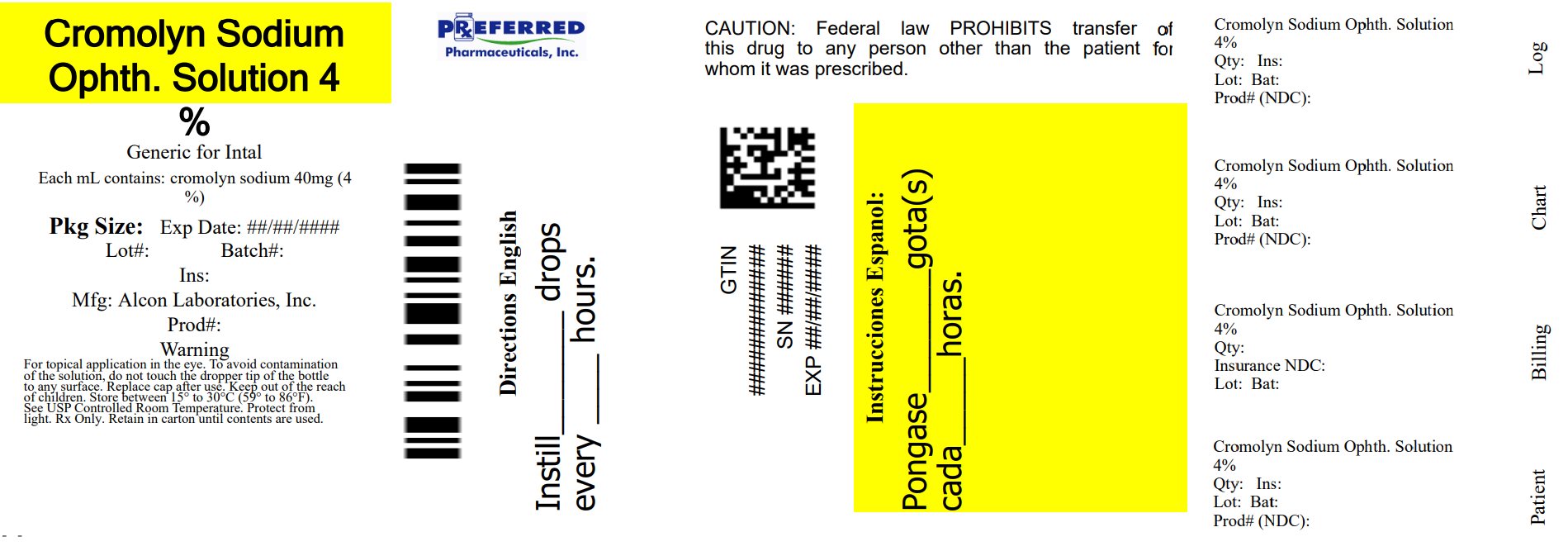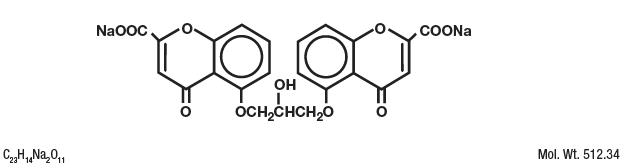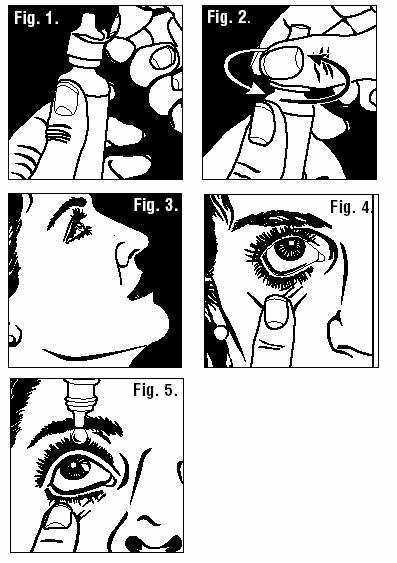 DRUG LABEL: Cromolyn Sodium
NDC: 68788-8490 | Form: SOLUTION/ DROPS
Manufacturer: Preferred Pharmaceuticals Inc.
Category: prescription | Type: HUMAN PRESCRIPTION DRUG LABEL
Date: 20250528

ACTIVE INGREDIENTS: CROMOLYN SODIUM 40 mg/1 mL
INACTIVE INGREDIENTS: BENZALKONIUM CHLORIDE; EDETATE DISODIUM; WATER; HYDROCHLORIC ACID; SODIUM HYDROXIDE

Cromolyn Sodium Ophthalmic Solution USP, 4%
Sterile

DESCRIPTION

Cromolyn Sodium Ophthalmic Solution USP, 4% is a clear, colorless, sterile solution intended for topical ophthalmic use.

Cromolyn sodium is represented by the following structural formula:

Chemical Name: Disodium 5-5'-[(2-hydroxytrimethylene)dioxy]bis[4-oxo-4H-1-benzopyran-2-carboxylate]

Pharmacologic Category: Mast cell stabilizer.

EACH mL CONTAINS: Active: cromolyn sodium 40 mg (4%); Preservative: benzalkonium chloride 0.01%. Inactives: edetate disodium 0.1% and purified water. Hydrochloric acid and/or sodium hydroxide may be added to adjust pH (4.0-7.0).

CLINICAL PHARMACOLOGY

In vitro and in vivo animal studies have shown that cromolyn sodium inhibits the degranulation of sensitized mast cells which occurs after exposure to specific antigens. Cromolyn sodium acts by inhibiting the release of histamine and SRS-A (slow-reacting substance of anaphylaxis) from the mast cell.

Another activity demonstrated in vitro is the capacity of cromolyn sodium to inhibit the degranulation of non-sensitized rat mast cells by phospholipase A and the subsequent release of chemical mediators. Another study showed that cromolyn sodium did not inhibit the enzymatic activity of released phospholipase A on its specific substrate.

Cromolyn sodium has no intrinsic vasoconstrictor, antihistaminic or anti-inflammatory activity.

Cromolyn sodium is poorly absorbed. When multiple doses of cromolyn sodium ophthalmic solution are instilled into normal rabbit eyes, less than 0.07% of the administered dose of cromolyn sodium is absorbed into the systemic circulation (presumably by way of the eye, nasal passages, buccal cavity and gastrointestinal tract). Trace amounts (less than 0.01%) of the cromolyn sodium dose penetrate into the aqueous humor and clearance from this chamber is virtually complete within 24 hours after treatment is stopped.

In normal volunteers, analysis of drug excretion indicates that approximately 0.03% of cromolyn sodium is absorbed following administration to the eye.

INDICATIONS AND USAGE

Cromolyn Sodium Ophthalmic Solution USP, 4% is indicated in the treatment of vernal keratoconjunctivitis, vernal conjunctivitis, and vernal keratitis.

CONTRAINDICATIONS

Cromolyn Sodium Ophthalmic Solution USP, 4% is contraindicated in those patients who have shown hypersensitivity to cromolyn sodium or to any of the other ingredients.

PRECAUTIONS

General

Patients may experience a transient stinging or burning sensation following application of Cromolyn Sodium Ophthalmic Solution USP, 4%.

The recommended frequency of administration should not be exceeded (see DOSAGE AND ADMINISTRATION).

Information for the Patient

Patients should be advised to follow the patient instructions listed on the Information for Patients sheet.

Users of contact lenses should refrain from wearing lenses while exhibiting the signs and symptoms of vernal keratoconjunctivitis, vernal conjunctivitis, or vernal keratitis. Do not wear contact lenses during treatment with Cromolyn Sodium Ophthalmic Solution USP, 4%.

Carcinogenesis, Mutagenesis, Impairment of Fertility

Long-term studies of cromolyn sodium in mice (12 months intraperitoneal administration at doses up to 150 mg/kg three days per week), hamsters (intraperitoneal administration at doses up to 52.6 mg/kg three days per week for 15 weeks followed by 17.5 mg/kg three days per week for 37 weeks), and rats (18 months subcutaneous administration at doses up to 75 mg/kg six days per week) showed no neoplastic effects. The average daily maximum dose levels administered in these studies were 192.9 mg/m^2 for mice, 47.2 mg/m^2 for hamsters and 385.8 mg/m^2 for rats. These doses correspond to approximately 6.8, 1.7 and 14 times the maximum daily human dose of 28 mg/m^2.

Cromolyn sodium showed no mutagenic potential in the Ames Salmonella/microsome plate assays, mitotic gene conversion in Saccharomycas cerevisiae and in an in vitro cytogenetic study in human peripheral lymphocytes.

No evidence of impaired fertility was shown in laboratory reproduction studies conducted subcutaneously in rats at the highest doses tested, 175 mg/kg/day (1050 mg/m^2) in males and 100 mg/kg/day (600 mg/m^2) in females. These doses are approximately 37 and 21 times the maximum daily human dose, respectively, based on mg/m^2.

Teratogenic Effects

Pregnancy Category B. Reproduction studies with cromolyn sodium administered subcutaneously to pregnant mice and rats at maximum daily doses of 540 mg/kg (1620 mg/m^2) and 164 mg/kg (984 mg/m^2), respectively, and intravenously to rabbits at a maximum daily dose of 485 mg/kg (5820 mg/m^2) produced no evidence of fetal malformation. These doses represent approximately 57, 35, and 205 times the maximum daily human dose, respectively, on a mg/m^2 basis. Adverse fetal effects (increased resorption and decreased fetal weight) were noted only at the very high parenteral doses that produced maternal toxicity. There are, however, no adequate and well-controlled studies in pregnant women. Because animal reproduction studies are not always predictive of human response, this drug should be used during pregnancy only if clearly needed.

Nursing Mothers

It is not known whether this drug is excreted in human milk. Because many drugs are excreted in human milk, caution should be exercised when Cromolyn Sodium Ophthalmic Solution USP, 4% is administered to a nursing woman.

Pediatric Use

Safety and effectiveness in children below the age of 4 years have not been established.

ADVERSE REACTIONS

The most frequently reported adverse reaction attributed to the use of cromolyn sodium ophthalmic solution, on the basis of reoccurrence following readministration, is transient ocular stinging or burning upon instillation.

The following adverse reactions have been reported as infrequent events. It is unclear whether they are attributable to the drug:

Conjunctival injection; watery eyes; itchy eyes; dryness around the eye; puffy eyes; eye irritation; and styes.

Immediate hypersensitivity reactions have been reported rarely and include dyspnea, edema and rash.

DOSAGE AND ADMINISTRATION

The dose is 1 or 2 drops in each eye 4 to 6 times a day at regular intervals. One drop contains approximately 1.6 mg cromolyn sodium.

Patients should be advised that the effect of cromolyn sodium ophthalmic solution therapy is dependent upon its administration at regular intervals, as directed.

Symptomatic response to therapy (decreased itching, tearing, redness, and discharge) is usually evident within a few days, but longer treatment for up to six weeks is sometimes required. Once symptomatic improvement has been established, therapy should be continued for as long as needed to sustain improvement.

If required, corticosteroids may be used concomitantly with Cromolyn Sodium Ophthalmic Solution USP, 4%.

HOW SUPPLIED

Cromolyn Sodium Ophthalmic Solution USP, 4% is supplied in a white, opaque, plastic ophthalmic dispenser in the following size:

10 mL NDC 68788-8490-1

Storage: Store between 15° - 30°C (59°- 86°F). Protect from light-store in original carton. Keep tightly closed and out of the reach of children.

Rx Only

300049857-0821

Manufactured by

Alcon Laboratories, Inc.

Fort Worth, Texas 76134 for

Sandoz Inc.

Princeton, NJ 08540

Printed in USA

August 2021

Relabeled By: Preferred Pharmaceuticals Inc.

Information for the Patient

Cromolyn Sodium (KRO moe lin SOE dee um) Ophthalmic Solution USP, 4%

Sterile

It is important to use Cromolyn Sodium Ophthalmic Solution USP, 4% regularly, as directed by your physician.

1. Thoroughly wash your hands.
2. Remove safety seal (Figure 1).
3. Remove cap (Figure 2).
4. Sit or stand comfortably, with your head tilted back (Figure 3).
5. Open eyes, look up, and draw the lower lid of your eye down gently with your index finger (Figure 4).
6. Hold the Cromolyn Sodium Ophthalmic Solution USP, 4% bottle upside down. Place dropper tip as close as possible to the lower eyelid and gently squeeze out the prescribed number of drops (Figure 5).
7. Do not touch the eye or eyelid with the dropper tip.
8. Blink a few times to make sure the eye is covered with the solution.
9. Close your eye and remove any excess solution with a clean tissue.
10. Repeat process in the other eye.

SPECIAL TIPS

1. Avoid placing Cromolyn Sodium Ophthalmic Solution USP, 4% directly on the cornea (the area just over the pupil), because it is especially sensitive. You will find the administration of the eye drops more comfortable if you place the drops just inside the lower eyelid as shown in Figure 5.
2. To avoid contamination of the solution, do not touch dropper tip to the eye, fingers, or any other surface. Replace cap after use. It is recommended that any remaining contents be discarded after the treatment period prescribed by your physician.
3. Store between 15°-30°C (59°-86°F). Protect from light - store in original carton.
4. Keep tightly closed and out of the reach of children.
5. Do not use with any other ocular medication unless directed by your physician. Do not wear contact lenses during treatment with Cromolyn Sodium Ophthalmic Solution USP, 4%.

Manufactured by

Alcon Laboratories, Inc.

Fort Worth, Texas 76134 for

Sandoz Inc.

Princeton, NJ 08540

Printed in USA

August 2021

300049857-0821

Relabeled By: Preferred Pharmaceuticals Inc.

PRINCIPAL DISPLAY PANEL

NDC 68788-8490-1

Cromolyn

Sodium

Ophthalmic

Solution USP

4%

Rx Only

STERILE

10 mL

SANDOZ

Relabeled By: Preferred Pharmaceuticals Inc.